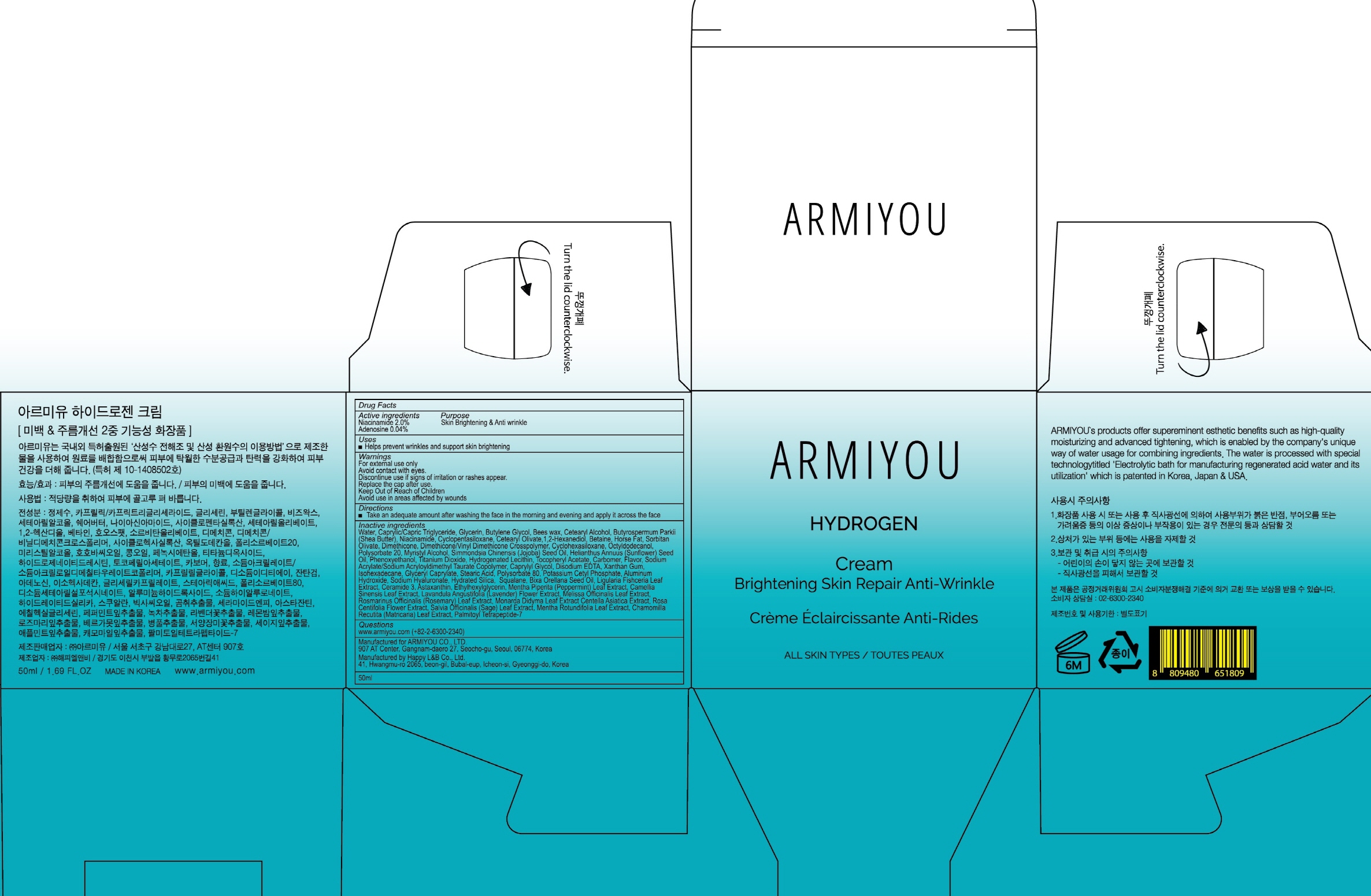 DRUG LABEL: ARMIYOU HYDROGEN
NDC: 71878-040 | Form: CREAM
Manufacturer: Armiyou
Category: otc | Type: HUMAN OTC DRUG LABEL
Date: 20171122

ACTIVE INGREDIENTS: Niacinamide 1.00 g/50 mL; Adenosine 0.02 g/50 mL
INACTIVE INGREDIENTS: Water; Butylene Glycol

ACTIVE INGREDIENT

Active ingredients: Niacinamide 2.0%, Adenosine 0.04%

INACTIVE INGREDIENT

Inactive ingredients: Water, Caprylic/Capric Triglyceride, Glycerin, Butylene Glycol, Bees wax, Cetearyl Alcohol, Butyrospermum Parkii (Shea Butter), Niacinamide, Cyclopentasiloxane, Cetearyl Olivate,1,2-Hexanediol, Betaine, Horse Fat, Sorbitan Olivate, Dimethicone, Dimethicone/Vinyl Dimethicone Crosspolymer, Cyclohexasiloxane, Octyldodecanol, Polysorbate 20, Myristyl Alcohol, Simmondsia Chinensis (Jojoba) Seed Oil, Helianthus Annuus (Sunflower) Seed Oil, Phenoxyethanol, Titanium Dioxide, Hydrogenated Lecithin, Tocopheryl Acetate, Carbomer, Flavor, Sodium Acrylate/Sodium Acryloyldimethyl Taurate Copolymer, Caprylyl Glycol, Disodium EDTA, Xanthan Gum, Isohexadecane, Glyceryl Caprylate, Stearic Acid, Polysorbate 80, Potassium Cetyl Phosphate, Aluminum Hydroxide, Sodium Hyaluronate, Hydrated Silica, Squalane, Bixa Orellana Seed Oil, Ligularia Fishceria Leaf Extract, Ceramide 3, Astaxanthin, Ethylhexylglycerin, Mentha Piperita (Peppermint) Leaf Extract, Camellia Sinensis Leaf Extract, Lavandula Angustifolia (Lavender) Flower Extract, Melissa Officinalis Leaf Extract, Rosmarinus Officinalis (Rosemary) Leaf Extract, Monarda Didyma Leaf Extract Centella Asiatica Extract, Rosa Centifolia Flower Extract, Salvia Officinalis (Sage) Leaf Extract, Mentha Rotundifolia Leaf Extract, Chamomilla Recutita (Matricaria) Leaf Extract, Palmitoyl Tetrapeptide-7

PURPOSE

Purpose: Skin Brightening & Anti wrinkle

WARNINGS

Warnings: For external use only Avoid contact with eyes. Discontinue use if signs of irritation or rashes appear. Replace the cap after use. Keep Out of Reach of Children. Avoid use in areas affected by wounds.

KEEP OUT OF REACH OF CHILDREN

Uses

Uses: Helps prevent wrinkles and support skin brightening

Directions

Directions: Take an adequate amount after washing the face in the morning and evening and apply it across the face.